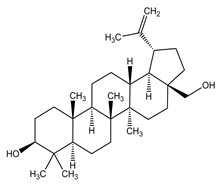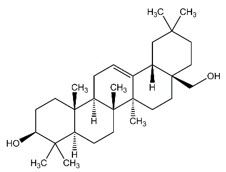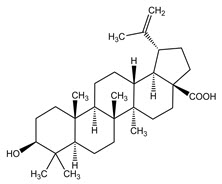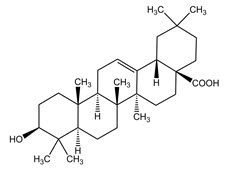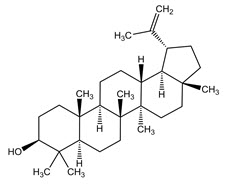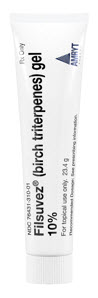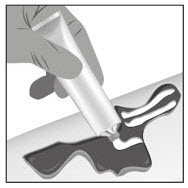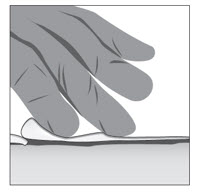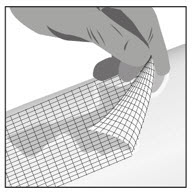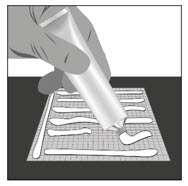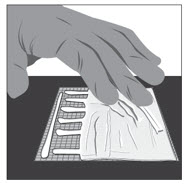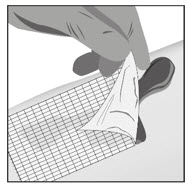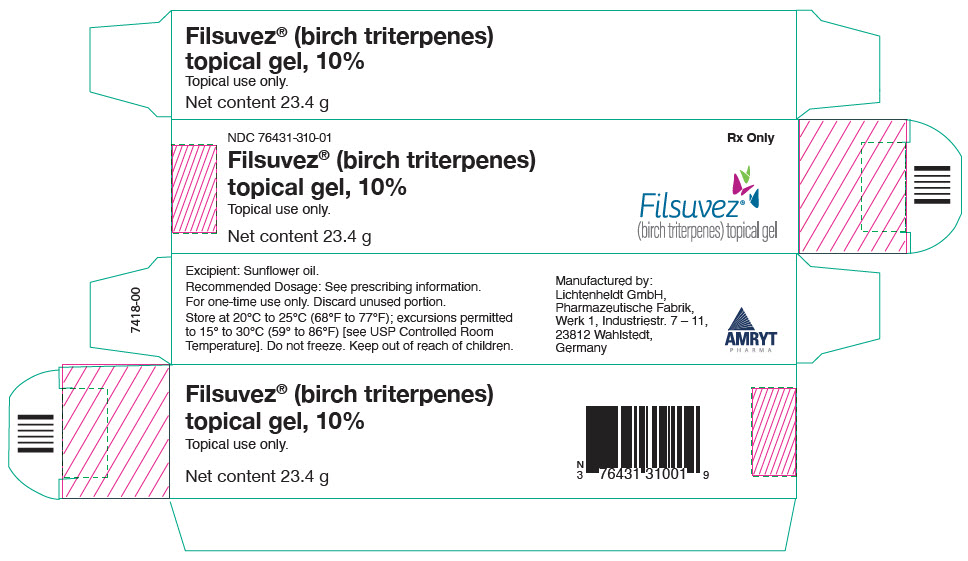 DRUG LABEL: FILSUVEZ
NDC: 76431-310 | Form: GEL
Manufacturer: Amryt Pharmaceuticals DAC
Category: prescription | Type: HUMAN PRESCRIPTION DRUG LABEL
Date: 20260120

ACTIVE INGREDIENTS: birch triterpenes 100 mg/1 g
INACTIVE INGREDIENTS: sunflower oil

HIGHLIGHTS OF PRESCRIBING INFORMATION

These highlights do not include all the information needed to use FILSUVEZ safely and effectively. See full prescribing information for FILSUVEZ.
FILSUVEZ® (birch triterpenes) topical gel
Initial U.S. Approval: 2023

1 INDICATIONS AND USAGE

FILSUVEZ topical gel is indicated for the treatment of wounds associated with dystrophic and junctional epidermolysis bullosa in adult and pediatric patients 6 months of age and older. (1)

2 DOSAGE AND ADMINISTRATION

- Apply a 1 mm layer of FILSUVEZ to the affected wound surface and cover with wound dressing or apply FILSUVEZ directly to dressing so that the topical gel is in direct contact with the wound. Do not rub in the topical gel. (2)
- Apply FILSUVEZ at wound dressing changes until the wound is healed. (2)
- Each tube of FILSUVEZ is for one-time use only. (2)
- For topical use; not for oral, intravaginal, intra-anal, or ophthalmic use. (2)

3 DOSAGE FORMS AND STRENGTHS

Topical gel: 10% birch triterpenes w/w supplied in 25 mL sterile tubes (3)

4 CONTRAINDICATIONS

None (4)

5 WARNINGS AND PRECAUTIONS

- Hypersensitivity Reactions: If signs or symptoms of hypersensitivity occur, discontinue use immediately and initiate appropriate therapy. (5.1)

6 ADVERSE REACTIONS

The most common (incidence ≥2%) adverse reactions are application site reactions. (6.1)

To report SUSPECTED ADVERSE REACTIONS, contact Amryt Pharmaceuticals DAC at 1-855-303-2347 or FDA at 1-800-FDA-1088 or www.fda.gov/medwatch.

FULL PRESCRIBING INFORMATION

1 INDICATIONS AND USAGE

FILSUVEZ is indicated for the treatment of wounds associated with dystrophic and junctional epidermolysis bullosa (EB) in adult and pediatric patients 6 months of age and older.

2 DOSAGE AND ADMINISTRATION

- Wash hands before and after applying FILSUVEZ or wear gloves for application.
- Apply a 1 mm layer of FILSUVEZ to the affected wound surface only. Do not rub in the gel. Cover the wound with a sterile non-adhesive wound dressing. Alternatively, apply FILSUVEZ directly to the dressing so that the topical gel is in direct contact with the wound.
- Apply FILSUVEZ to cleansed wounds with wound dressing changes until the wound is healed.
- If a FILSUVEZ-treated wound becomes infected, discontinue treatment to that wound until the infection has resolved.
- Each tube of FILSUVEZ is for one-time use only. Once the tube is opened, use the product immediately. Discard the tube after use in household trash or through a drug take back site, if available.
- Avoid contact of FILSUVEZ with eyes and mucous membranes (e.g., mouth, vagina, anus). In case of accidental contact, irrigate the area with water.
- FILSUVEZ is for topical use only. Not for use on mucous membranes (oral, intravaginal, or intra-anal). Not for ophthalmic use.

3 DOSAGE FORMS AND STRENGTHS

Topical gel: 10% birch triterpenes w/w in a colorless to slightly yellowish, opalescent, non-aqueous gel supplied in 25 mL sterile tubes.

4 CONTRAINDICATIONS

None.

5 WARNINGS AND PRECAUTIONS

5.1 Hypersensitivity Reactions

Local hypersensitivity and skin reactions have been reported in patients treated with FILSUVEZ, including urticaria and dermatitis.

If signs and symptoms of local or systemic hypersensitivity occur, discontinue FILSUVEZ immediately and initiate appropriate therapy.

6 ADVERSE REACTIONS

The following clinically significant adverse reactions are discussed elsewhere in the labeling:

- Hypersensitivity Reactions [see Warnings and Precautions (5.1)]

6.1 Clinical Trials Experience

Because clinical trials are conducted under widely varying conditions, adverse reaction rates observed in the clinical trials of a drug cannot be directly compared to rates in the clinical trials of another drug and may not reflect the rates observed in practice.

The safety of FILSUVEZ was evaluated in EASE, a randomized, double-blind, multicenter, placebo-controlled trial in 223 adult and pediatric subjects with inherited EB. During the double-blind phase of EASE, subjects received topical treatment with either FILSUVEZ or a placebo gel on partial-thickness wounds every 1 to 4 days for a total of 90 days. Treated wounds were covered with non-adhesive dressings. Following completion of the double-blind phase, all subjects received FILSUVEZ for a total of 24 months during the open-label phase [see Clinical Studies (14)].

Table 1 presents adverse reactions that occurred in at least 2% of subjects treated with FILSUVEZ during the 90-day double-blind phase of EASE and at a greater frequency than in the placebo gel group.

Table 1: Number (%) of Subjects with Adverse Reactions Occurring in ≥ 2%
Adverse Reaction | FILSUVEZ (N=109) n (%) | Placebo Gel (N=114) n (%)
Application site reaction [Includes: application site pruritus, administration site pain, administration site pruritus.] | 8 (7.3) | 7 (6.1)

Squamous cell carcinoma of the skin (SCC) was reported as an adverse event in the double-blind and open-label periods of EASE. Four subjects with recessive dystrophic EB each reported one SCC: a 20-year-old male on day 1 of the double-blind period; three female subjects ages 22, 46, and 49 years during the open-label period. Two of the four subjects had applied FILSUVEZ to the area which developed the SCC.

8 USE IN SPECIFIC POPULATIONS

8.1 Pregnancy

Risk Summary

There are no available data with use of FILSUVEZ in pregnant women to evaluate for drug-associated risk of major birth defects, miscarriage or adverse maternal or fetal outcomes. In an animal reproduction study, oral administration of birch triterpenes to pregnant rats during the period of organogenesis had no effects on reproductive or fetal parameters (see Data).

Systemic absorption of FILSUVEZ in humans is low following topical administration of FILSUVEZ, and maternal use is not expected to result in fetal exposure to the drug [see Pharmacokinetics (12.3)].

The background risk of major birth defects and miscarriage for the indicated population is unknown. In the U.S. general population, the estimated background risk of major birth defects and miscarriage in clinically recognized pregnancies is 2% to 4% and 15% to 20%, respectively.

Data

Animal Data

In an embryofetal development study, birch triterpenes were orally administered to pregnant rats at doses of 10, 30, or 100 mg/kg/day during the period of organogenesis. Birch triterpenes did not cause maternal toxicity or fetal malformations at doses up to 100 mg/kg/day. In a prenatal and postnatal development study, birch triterpenes were orally administered to pregnant rats at doses of 10, 30, or 100 mg/kg/day from gestation day 5 through lactation day 20. Birch triterpenes did not affect development at doses up to 100 mg/kg/day. The available data do not support relevant comparisons of systemic birch triterpenes exposures achieved in the animal studies to exposures observed in humans after topical use of FILSUVEZ.

8.2 Lactation

Risk Summary

There are no data on the presence of birch triterpenes or metabolites in human milk, the effects on the breastfed infant, or the effect on milk production.

No effects on the breastfed infant are anticipated since the systemic exposure of the breastfeeding woman to FILSUVEZ would be low. Therefore, the developmental and health benefits of breastfeeding should be considered along with the mother's clinical need for FILSUVEZ and any potential adverse effects on the breastfed infant from FILSUVEZ or from the underlying maternal condition [see Pharmacokinetics (12.3)].

8.4 Pediatric Use

The safety and effectiveness of FILSUVEZ for the treatment of wounds associated with dystrophic and junctional EB have been established in pediatric patients 6 months of age and older. Use of FILSUVEZ in this age group is supported by evidence from a single randomized, placebo-controlled trial in 156 subjects 6 months to 17 years of age [see Clinical Studies (14)].

The safety and effectiveness of FILSUVEZ have not been established in pediatric patients younger than 6 months of age.

8.5 Geriatric Use

Clinical studies of FILSUVEZ did not include sufficient numbers of EB subjects 65 years of age and older to determine whether they respond differently from younger subjects.

11 DESCRIPTION

FILSUVEZ (birch triterpenes) topical gel is a sterile botanical drug product for topical use and contains birch triterpenes in an oil base. FILSUVEZ is a colorless to slightly yellowish, opalescent, non-aqueous gel.

Birch triterpenes is a botanical drug substance composed of a mixture of pentacyclic triterpenes. The botanical drug substance is a dry extract, refined, from birch bark from Betula pendula Roth, Betula pubescens Ehrh., as well as hybrids of both species, quantified to 72-88% (w/w) betulin, 2.4-5.7% (w/w) lupeol, 2.6-4.2% (w/w) betulinic acid, 0.5-1.2% (w/w) erythrodiol, 0.3-0.8% (w/w) oleanolic acid.

The structural formulae of the main triterpene constituents are shown in Figure 1.

Figure 1: Structure of Triterpene Constituents

Betulin |  | Erythrodiol
Betulinic acid |  | Oleanolic acid
Lupeol

Each gram of FILSUVEZ topical gel 10% (w/w) contains 100 mg of birch triterpenes in an oil base of refined sunflower oil. FILSUVEZ contains no additional excipients.

12 CLINICAL PHARMACOLOGY

12.1 Mechanism of Action

The mechanism of action of FILSUVEZ in the treatment of wounds associated with epidermolysis bullosa is unknown.

12.2 Pharmacodynamics

Pharmacodynamics of FILSUVEZ are unknown.

12.3 Pharmacokinetics

Absorption

Systemic exposure to betulin was assessed in the 66 evaluable subjects aged ≥13 months to ≤52 years with dystrophic and junctional EB in the clinical trial EASE using venous blood sampling and validated liquid chromatography with tandem mass spectrometry assay.

Following treatment with FILSUVEZ once daily (n=27), every 2 (n=33) or 3 days (n=4) or once weekly (n=2) for 90 days with a mean treatment area of 12% body surface area or affected wound surface area of 0.11 m^2 at baseline, betulin blood concentrations in 68% subjects (n=45) were below the lower limit of quantification of 10 ng/mL on Day 90. The highest concentrations of betulin in adult and pediatric subjects with a median age of 10 years (range: ≥13 months to <18 years) were 33 ng/mL and 207 ng/mL, respectively, which were observed on Day 90.

Distribution

Plasma protein binding of betulin in vitro is >99.9 %.

Metabolism

The in vitro study indicated that incubation of 1 µmol/L betulin with human hepatocytes generated several unidentified phase I and/or phase II metabolites. In vitro, betulin was mainly metabolized by cytochrome P450 (CYP)3A. The relative contribution of CYP3A and phase II metabolizing enzymes in the overall metabolism of betulin has not been fully characterized.

Drug Interaction Studies

Clinical Studies

No clinical studies evaluating the drug interaction potential of FILSUVEZ have been conducted.

In Vitro Studies

CYP Enzymes: Betulin inhibited CYP3A and CYP2C8 with an IC50 value of >0.17 µmol/L (75 ng/mL). Betulin up to 10 µmol/L (4427 ng/mL) did not induce CYP 1A2, 2B6, or 3A4. These findings suggest that FILSUVEZ has no clinically meaningful effect on the PK of drugs metabolized by CYP 1A2, 2B6, 2C8, 2C9, 2C19, 2D6, or 3A.

13 NONCLINICAL TOXICOLOGY

13.1 Carcinogenesis, Mutagenesis, Impairment of Fertility

No carcinogenicity studies have been performed with FILSUVEZ or birch triterpenes.

Birch triterpenes were not genotoxic in the in vitro bacterial mutagenicity (Ames) assay, an in vitro mammalian chromosome aberration assay using human peripheral lymphocytes, or at doses up to 500 mg/kg in an in vivo mouse micronucleus assay.

In a fertility and early embryonic development study in rats, birch triterpenes were orally administered at doses of 10, 30, or 100 mg/kg/day from 2 weeks before mating through gestation day 6. Birch triterpenes had no effects on mating or fertility in male or female rats at doses up to 100 mg/kg/day.

14 CLINICAL STUDIES

The efficacy of FILSUVEZ for the treatment of partial-thickness wounds associated with inherited EB was evaluated in a randomized, double-blind, placebo-controlled trial in adults and pediatric subjects 6 months of age and older (EASE; NCT03068780) with dystrophic EB (DEB) and junctional EB (JEB). Subjects were randomized 1:1 to receive FILSUVEZ (n=109) or placebo topical gel (n=114) and instructed to apply approximately 1 mm (0.04 inch) of the investigational product to all their wounds at each dressing change (every 1 to 4 days) for 90 days. At randomization, 1 wound was selected by the investigator as the target wound for the evaluation of the primary efficacy endpoint. The target wound was defined as a partial-thickness wound of 10-50 cm^2 in surface area and present for 21 days to 9 months prior to screening.

Of the 223 subjects randomized, the median age was 12 years (range: 6 months to 81 years), 70% were under 18 years of age, and 60% were male and 40% were female. Eighty three (83)% of subjects were White, 5% were Asian, 1% were Black or African American, and 10% were other races or did not have race recorded. For ethnicity, 35% identified as Hispanic or Latino and 65% identified as not Hispanic or Latino. Of these 223 subjects, 195 had DEB, of which 175 subjects had recessive DEB (RDEB) and 20 had dominant DEB (DDEB); in addition, there were 26 subjects with JEB and 2 subjects with EB simplex.

The primary endpoint was the proportion of subjects with first complete closure of the target wound by Day 45 of the 90-day double-blind phase of the study, based on clinical assessment by the investigator. Efficacy results from EASE are presented in Table 2.

Table 2: Efficacy Results for the Treatment of Partial-Thickness Wounds in Subjects with EB in Trial EASE (Full Analysis Set)
Efficacy Parameter | FILSUVEZ N=109 | Placebo Gel N=114 | 95% CI for the Treatment Difference
Proportion of subjects with first complete closure of target wound within 45 days | 41.3% | 28.9% | (0.8, 25.6)
By EB subtype [Two subjects with EB simplex are not included]
RDEB (n=175) | 44.0% | 26.2% | (3.9, 31.6)
DDEB (n=20) | 50.0% | 50.0% | (-47.8, 47.8)
JEB (n=26) | 18.2% | 26.7% | (-40.4, 23.5)
Proportion of subjects with first complete closure of target wound within 90 days | 50.5% | 43.9% | (-6.2, 20.0)
CI=Confidence interval

16 HOW SUPPLIED/STORAGE AND HANDLING

FILSUVEZ (birch triterpenes) topical gel, 10% (w/w) is a colorless to slightly yellowish, opalescent, non-aqueous gel and is supplied in 25 mL white aluminum tubes containing 23.4 grams of gel per tube (NDC 76431-310-01).

Each sterile tube is for one-time use only. Once opened, the product should be used immediately and discarded after use.

STORAGE AND HANDLING

Store at 20°C to 25°C (68° F to 77°F); excursions permitted to 15° to 30°C (59° to 86°F) [see USP Controlled Room Temperature]).

Do not freeze.

Do not use beyond the expiration date.

17 PATIENT COUNSELING INFORMATION

Advise the patient to read the FDA-approved patient labeling (Patient Information and Instructions for Use).

Administration Instructions

Advise patients (and/or their caregivers or guardians) of the following [see Dosage and Administration (2)]:

- Wash hands before and after applying FILSUVEZ or wear gloves for application.
- Apply a 1 mm layer of FILSUVEZ to the affected wound surface. Do not rub in the gel. Cover the wound with a sterile non-adhesive wound dressing. Alternatively, apply a generous layer of FILSUVEZ directly to the dressing so that the gel is in direct contact with the wound.
- Apply FILSUVEZ to cleansed wounds at dressing changes until the wound is healed.
- FILSUVEZ is for topical use only. FILSUVEZ is not for ophthalmic use and should not be applied to mucous membranes. In case of accidental contact, irrigate eyes with water.
- The sterile tube of topical gel is for one-time use only. Once the tube is opened, use the product immediately. Discard the tube after use, even if there is some topical gel left.

Hypersensitivity Reactions

- Inform patients that local hypersensitivity and skin reactions, including urticaria and dermatitis, have been reported in patients treated with FILSUVEZ. If signs and symptoms of local hypersensitivity or skin reactions occur, instruct patients to discontinue FILSUVEZ immediately and contact their healthcare provider [see Warnings and Precautions (5.1)].

Manufactured by:

Lichtenheldt GmbH
Pharmazeutische Fabrik
Werk 1
Industriestr. 7-11
23812 Wahlstedt
Germany

PATIENT INFORMATION
FILSUVEZ (fill-sue-vez)
(birch triterpenes) topical gel

Important information: FILSUVEZ is for use on the skin (topical use) only. Do not use FILSUVEZ in your eyes, mouth, vagina or anus.

What is FILSUVEZ?
FILSUVEZ is a prescription medicine used on the skin to treat wounds that may happen with dystrophic and junctional epidermolysis bullosa (EB) in adults and children 6 months of age and older.
It is not known if FILSUVEZ is safe and effective in children younger than 6 months of age.

Do not use FILSUVEZ if you are allergic to any of its ingredients. See the end of this leaflet for a complete list of ingredients in FILSUVEZ.

Before using FILSUVEZ, tell your healthcare provider about all of your medical conditions, including if you:

- are pregnant or plan to become pregnant. It is not known if FILSUVEZ will harm your unborn baby.
- are breastfeeding or plan to breastfeed. It is not known if FILSUVEZ passes into your breast milk.

Tell your healthcare provider about all the medicines you take, including prescription and over-the-counter medicines, vitamins and herbal supplements.

How should I use FILSUVEZ?
See the detailed "Instructions for Use" that comes with FILSUVEZ for information on how to apply FILSUVEZ.

- Use FILSUVEZ exactly as your healthcare provider tells you to use it.
- Clean wounds before applying FILSUVEZ as instructed by your healthcare provider.
- Wash hands before applying FILSUVEZ or wear gloves.
- Apply FILSUVEZ at each dressing change until the wound is healed.
- Check the expiration date on the FILSUVEZ tube. Do not use FILSUVEZ if the expiration date has passed. Call your pharmacist or healthcare provider for instructions.
- The tube of FILSUVEZ is for one-time use only. After the tube has been opened, apply the gel right away. Throw away any remaining gel and the tube after use.
- Wash hands after applying FILSUVEZ and caring for wounds.
- Do not use around or get FILSUVEZ in the eyes, or mucous membrane areas examples are mouth, vagina or anus.
- If you get FILSUVEZ in your eyes or mucous membrane area, rinse with clean water right away. Contact your healthcare provider if you have any discomfort.
- If the wounds you are treating with FILSUVEZ become infected, stop treatment and contact your healthcare provider. Signs or symptoms of infection may include the wound becoming red, warm, swollen, painful or drains yellow or greenish fluid (pus).

What are the possible side effects of FILSUVEZ?
FILSUVEZ may cause serious side effects including:

- Allergic reactions. Allergic reactions and skin reactions to FILSUVEZ may include the following symptoms: red itchy bumps (hives), skin rash, redness or itching. If you get any of these symptoms, stop using FILSUVEZ right away and call your healthcare provider.

The most common side effect of FILSUVEZ is application site reactions, such as pain and itchy skin.
These are not all the possible side effects of FILSUVEZ.
Call your doctor for medical advice about side effects. You may report side effects to FDA at 1-800-FDA-1088.

How should I store FILSUVEZ?

- Store FILSUVEZ at room temperature between 68°F to 77°F (20°C to 25°C). Do not freeze.
- FILSUVEZ is for one-time use only. Throw away (dispose of) any remaining FILSUVEZ and the tube right away after use in household trash or through a drug take-back option, if available. Go to www.fda.gov/drugdisposal for more information on drug disposal.

Keep FILSUVEZ and all medicines out of the reach of children.

General information about the safe and effective use of FILSUVEZ
Medicines are sometimes prescribed for purposes other than those listed in a Patient Information leaflet. Do not use FILSUVEZ for a condition for which it was not prescribed. Do not give FILSUVEZ to other people, even if they have the same symptoms that you have. It may harm them. You can ask your pharmacist or healthcare provider for information about FILSUVEZ that is written for healthcare professionals.

What are the ingredients in FILSUVEZ?
Active ingredient: birch triterpenes
Inactive ingredients: refined sunflower oil
Manufactured by: Lichtenheldt GmbH, Pharmazeutische Fabrik, Werk 1, Industriestr. 7-11, 23812 Wahlstedt, Germany.
For more information, call 1-855-303-2347 or go to www.filsuvez.com

This Patient Information has been approved by the U.S. Food and Drug Administration

Issued: 12/2023

INSTRUCTIONS FOR USE FILSUVEZ (fill-sue-vez) (birch triterpenes) topical gel

Important information: FILSUVEZ is for use on the skin (topical use) only. Do not use FILSUVEZ in or around your eyes or mucous membranes (for example, the mouth, vagina, or anus).

This Instructions for Use contains information on how to apply FILSUVEZ. Read this Instructions for Use before you start using FILSUVEZ. Ask your healthcare provider if you have any questions.

Important Information You Need to Know Before Applying FILSUVEZ

- Use FILSUVEZ exactly as your healthcare provider tells you to use it.
- Apply FILSUVEZ directly to the wound or to the dressing surface that will be in contact with the wound.
- Clean wounds before applying FILSUVEZ as instructed by your healthcare provider.
- Apply FILSUVEZ with a clean or gloved hand.
- Apply FILSUVEZ at each dressing change until the wound is completely healed.
- Do not get FILSUVEZ in or apply around the eyes, or mucous membranes (For example, mouth, vagina, or anus). If you get FILSUVEZ in your eyes or mucous membranes, rinse with clean water right away. Contact your healthcare provider if you have any discomfort.
- Wash hands after applying FILSUVEZ and caring for wounds.
- The tube of FILSUVEZ is for one-time use only. After the tube has been opened, apply the FILSUVEZ gel right away. Throw away any remaining gel and the tube after use.
- Check the expiration date on the FILSUVEZ tube. Do not use FILSUVEZ if the expiration date has passed. Call your pharmacist or healthcare provider for instructions.

Gather your supplies

- a new tube of FILSUVEZ
- gloves (if using)
- sterile, non-adhesive dressing

Applying FILSUVEZ

- Wash your hands with soap and water or wear gloves.
- Open a new tube of FILSUVEZ. Apply the gel right away.
- You can apply FILSUVEZ in 2 ways, either directly to the wound or to the non-adhesive dressing surface that will be in contact with the wound.
  Option 1: Apply FILSUVEZ directly to wound.
  - Apply a 1 mm layer of FILSUVEZ to the wound (See Step 1). Cover the entire wound surface with a 1 mm layer of FILSUVEZ (Step 2). Do not rub in the gel. Cover the wound with a sterile, non-adhesive wound dressing (see Step 3).
  Step 1
  Step 2
  Step 3
  or
  Option 2: Apply FILSUVEZ directly to sterile, non-adhesive dressing.
  - Apply a generous layer of FILSUVEZ directly to the sterile, non-adhesive dressing (see Step 1). Cover the entire non-adhesive dressing with FILSUVEZ (Step 2). Cover the wound with the dressing so that the gel is in direct contact with the wound (see Step 3). Secure the non-adhesive wound dressing as directed by your healthcare provider .
  Step 1
  Step 2
  Step 3

How should I store FILSUVEZ?

Store FILSUVEZ at room temperature between 68°F to 77°F (20°C to 25°C). Do not freeze.

Keep FILSUVEZ and all medicines out of the reach of children.

How should I throw away (dispose of) FILSUVEZ?

Throw away (dispose of) any remaining FILSUVEZ and the tube right away after use in household trash or through a drug take-back option, if available. Go to www.fda.gov/drugdisposal for more information on drug disposal.

Manufactured by: Lichtenheldt GmbH, Pharmazeutische Fabrik, Werk 1, Industriestr. 7-11, 23812 Wahlstedt, Germany

For more information, call 1-855-303-2347 or go to www.filsuvez.com

This Instructions for Use has been approved by the U.S. Food and Drug Administration. Approved: December-2023

PRINCIPAL DISPLAY PANEL - 23.4 g Tube Carton

NDC 76431-310-01

Rx Only

Filsuvez® (birch triterpenes)
topical gel, 10%

Topical use only.

Net content 23.4 g

Filsuvez®
(birch triterpenes) topical gel